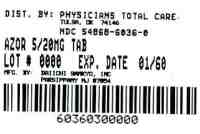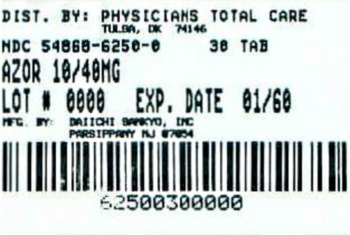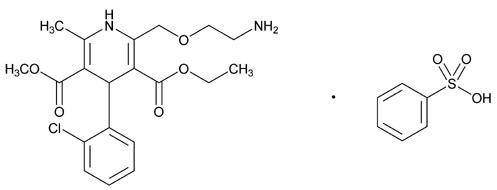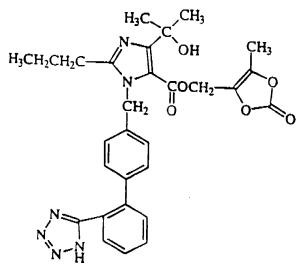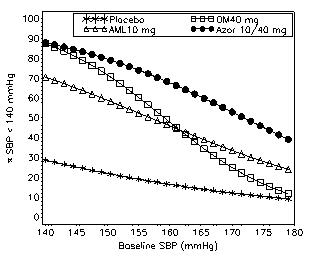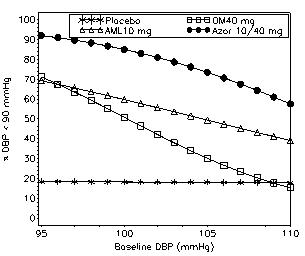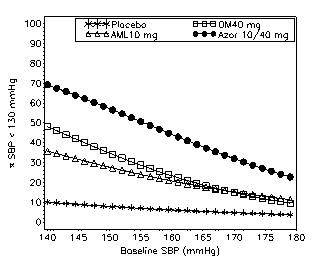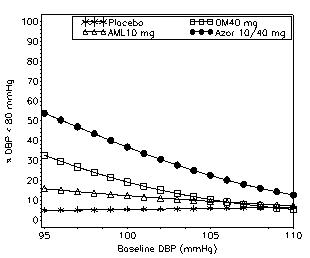 DRUG LABEL: Azor
NDC: 54868-6036 | Form: TABLET, FILM COATED
Manufacturer: Physicians Total Care, Inc.
Category: prescription | Type: HUMAN PRESCRIPTION DRUG LABEL
Date: 20120109

ACTIVE INGREDIENTS: AMLODIPINE BESYLATE 5 mg/1 1; OLMESARTAN MEDOXOMIL 20 mg/1 1
INACTIVE INGREDIENTS: CELLULOSE, MICROCRYSTALLINE; STARCH, CORN; CROSCARMELLOSE SODIUM; MAGNESIUM STEARATE; POLYVINYL ALCOHOL; POLYETHYLENE GLYCOL 3350; TITANIUM DIOXIDE; TALC

HIGHLIGHTS OF PRESCRIBING INFORMATION

These highlights do not include all the information needed to use Azor safely and effectively. See full prescribing information for Azor. Azor (amlodipine and olmesartan medoxomil) tablet, film coated for oral use Initial U.S. Approval: 2007

BOXED WARNING

USE IN PREGNANCY
See full prescribing information for complete boxed warning.
When pregnancy is detected, discontinue Azor as soon as possible. When used in pregnancy during the second and third trimesters, drugs that act directly on the renin-angiotensin system can cause injury and even death to the developing fetus (5.1).

RECENT MAJOR CHANGES

Indications and Usage (1) 11/2011

1 INDICATIONS AND USAGE

- Azor is a dihydropyridine calcium channel blocker and angiotensin II receptor blocker combination product indicated for the treatment of hypertension, alone or with other antihypertensive agents, to lower blood pressure. Lowering blood pressure reduces the risk of fatal and nonfatal cardiovascular events, primarily strokes and myocardial infarctions. (1).
- Azor is indicated as initial therapy in patients likely to need multiple antihypertensive agents to achieve their blood pressure goals (1).

2 DOSAGE AND ADMINISTRATION

- Substitute Azor for its individually titrated components for patients on amlodipine and olmesartan medoxomil. Azor may also be given with increased amounts of amlodipine, olmesartan medoxomil, or both, as needed (2).
- Azor may be used to provide additional blood pressure lowering for patients not adequately controlled with amlodipine (or another dihydropyridine calcium channel blocker) alone or with olmesartan medoxomil (or another angiotensin receptor blocker) alone (2).
- Dosage may be increased after 2 weeks to a maximum dose of 10/40 mg once daily, usually by increasing one component at a time but both components can be raised to achieve more rapid control (2).
- Maximum antihypertensive effects are attained within 2 weeks after a change in dose (2).
- Initial therapy: Initiate with 5/20 mg once daily for 1 to 2 weeks and titrate as needed up to a maximum of 10/40 mg once daily (2).

3 DOSAGE FORMS AND STRENGTHS

Tablets: (amlodipine/olmesartan medoxomil content) 5/20 mg; 10/20mg; 5/40 mg; and 10/40 mg (3).

4 CONTRAINDICATIONS

None (4).

5 WARNINGS AND PRECAUTIONS

- Hypotension in volume- or salt-depleted patients with treatment initiation may be anticipated. Start treatment under close supervision (5.2).
- Increased angina or myocardial infarction with calcium channel blockers may occur upon dosage initiation or increase (5.4).
- Impaired renal function: changes in renal function may be anticipated in susceptible individuals (5.6).

6 ADVERSE REACTIONS

Most common adverse reaction (incidence ≥3%) is edema (6.1).

To report SUSPECTED ADVERSE REACTIONS, contact Daiichi Sankyo, Inc. at 1-877-437-7763 or FDA at 1-800-FDA-1088 or www.fda.gov/medwatch

8 USE IN SPECIFIC POPULATIONS

- In patients with an activated renin-angiotensin system, such as volume- or salt-depletion, renin-angiotensin-aldosterone system (RAAS) blockers such as olmesartan medoxomil can cause excessive hypotension. In susceptible patients, e.g. with renal artery stenosis, RAAS blockers can cause renal failure (5.2, 5.6).
- Start amlodipine alone or add amlodipine at 2.5 mg in patients ≥75 years old or in hepatically impaired patients. Elderly and patients with hepatic impairment have decreased clearance of amlodipine. Initial therapy with Azor is not recommended in patients ≥75 years old or hepatically impaired patients (8.5, 8.6).

FULL PRESCRIBING INFORMATION

BOXED WARNING

Azor®
(amlodipine and olmesartan medoxomil) tablets

USE IN PREGNANCY

When pregnancy is detected, discontinue Azor as soon as possible. When used in pregnancy during the second and third trimesters, drugs that act directly on the renin-angiotensin system can cause injury and even death to the developing fetus [see Warning and Precautions (5.1)].

RECENT MAJOR CHANGES

Enter section text here

1 INDICATIONS AND USAGE

Azor is indicated for the treatment of hypertension, alone or with other antihypertensive agents , to lower blood pressure. Lowering blood pressure reduces the risk of fatal and nonfatal cardiovascular events, primarily strokes and myocardial infarctions. These benefits have been seen in controlled trials of antihypertensive drugs from a wide variety of pharmacologic classes including the class to which this drug principally belongs. There are no controlled trials demonstrating risk reduction with Azor.

Control of high blood pressure should be part of comprehensive cardiovascular risk management, including, as appropriate, lipid control, diabetes management, antithrombotic therapy, smoking cessation, exercise, and limited sodium intake. Many patients will require more than one drug to achieve blood pressure goals. For specific advice on goals and management, see published guidelines, such as those of the National High Blood Pressure Education Program’s Joint National Committee on Prevention, Detection, Evaluation, and Treatment of High Blood Pressure (JNC).

Numerous antihypertensive drugs, from a variety of pharmacologic classes and with different mechanisms of action, have been shown in randomized controlled trials to reduce cardiovascular morbidity and mortality, and it can be concluded that it is blood pressure reduction, and not some other pharmacologic property of the drugs, that is largely responsible for those benefits. The largest and most consistent cardiovascular outcome benefit has been a reduction in the risk of stroke, but reductions in myocardial infarction and cardiovascular mortality also have been seen regularly.

Elevated systolic or diastolic pressure causes increased cardiovascular risk, and the absolute risk increase per mmHg is greater at higher blood pressures, so that even modest reductions of severe hypertension can provide substantial benefit. Relative risk reduction from blood pressure reduction is similar across populations with varying absolute risk, so the absolute benefit is greater in patients who are at higher risk independent of their hypertension (for example, patients with diabetes or hyperlipidemia), and such patients would be expected to benefit from more aggressive treatment to a lower blood pressure goal.

Some antihypertensive drugs have smaller blood pressure effects (as monotherapy) in black patients, and many antihypertensive drugs have additional approved indications and effects (e.g., on angina, heart failure, or diabetic kidney disease). These considerations may guide selection of therapy.

Azor may also be used as initial therapy in patients who are likely to need multiple antihypertensive agents to achieve their blood pressure goals.

Patients with moderate or severe hypertension are at relatively high risk for cardiovascular events (such as strokes, heart attacks, and heart failure), kidney failure, and vision problems, so prompt treatment is clinically relevant. The decision to use a combination as initial therapy should be individualized and should be shaped by considerations such as baseline blood pressure, the target goal, and the incremental likelihood of achieving goal with a combination compared to monotherapy. Individual blood pressure goals may vary based upon the patient’s risk.

Data from an 8-week, placebo-controlled, parallel-group factorial study [see Clinical Studies (14.1)] provide estimates of the probability of reaching a blood pressure goal with Azor compared to amlodipine or olmesartan medoxomil monotherapy. The figures below provide estimates of the likelihood of achieving the targeted systolic or diastolic blood pressure goals with Azor 10/40 mg compared with amlodipine or olmesartan medoxomil monotherapy, based upon baseline systolic or diastolic blood pressure. The curve of each treatment group was estimated by logistic regression modeling from all available data of that treatment group. The right tail of each curve is less reliable because of small numbers of subjects with high baseline blood pressures.

Figure 1: Probability of Achieving Systolic Blood Pressure (SBP) <140 mmHg at Week 8 With LOCF

Figure 2: Probability of Achieving Diastolic Blood Pressure (DBP) <90 mmHg at Week 8 With LOCF

Figure 3: Probability of Achieving Systolic Blood Pressure (SBP) <130 mmHg at Week 8 With LOCF

Figure 4: Probability of Achieving Diastolic Blood Pressure (DBP) <80 mmHg at Week 8 With LOCF

The figures above provide an approximation of the likelihood of reaching a targeted blood pressure goal (e.g., Week 8 SBP <140 mmHg or <130 mmHg or a DBP <90 mmHg or <80 mmHg) for the high-dose treatment groups evaluated in the study. Azor 5/20 mg, the lowest dose combination treatment group, increases the probability of reaching blood pressure goal compared with the highest dose monotherapies, amlodipine 10 mg and olmesartan medoxomil 40 mg.

For example, a patient with a baseline blood pressure of 160/100 mmHg has about a 48% likelihood of achieving a goal of <140 mmHg (systolic) and a 51% likelihood of achieving a goal of <90 mmHg (diastolic) on monotherapy with olmesartan medoxomil 40 mg, and about a 46% likelihood of achieving a goal of <140 mmHg (systolic) and a 60% likelihood of achieving a goal of <90 mmHg (diastolic) on monotherapy with amlodipine 10 mg. The likelihood of achieving these same goals increases to 63% (systolic) and 71% (diastolic) on Azor 5/20 mg, and to 68% (systolic) and 85% (diastolic) on Azor 10/40 mg.

2 DOSAGE AND ADMINISTRATION

General Considerations

The side effects of olmesartan medoxomil are generally rare and apparently independent of dose. Those of amlodipine are generally dose-dependent (mostly edema).

Maximum antihypertensive effects are attained within 2 weeks after a change in dose.

Azor may be taken with or without food.

Azor may be administered with other antihypertensive agents.

Dosage may be increased after 2 weeks. The maximum recommended dose of Azor is 10/40 mg.

Replacement Therapy

Azor may be substituted for its individually titrated components.

When substituting for individual components, the dose of one or both of the components can be increased if blood pressure control has not been satisfactory.

Add-on Therapy

Azor may be used to provide additional blood pressure lowering for patients not adequately controlled with amlodipine (or another dihydropyridine calcium channel blocker) alone or with olmesartan medoxomil (or another angiotensin receptor blocker) alone.

Initial Therapy

The usual starting dose of Azor is 5/20 mg once daily. The dosage can be increased after 1 to 2 weeks of therapy to a maximum dose of one 10/40 mg tablet once daily as needed to control blood pressure [See Clinical Studies (14.1)].

Initial therapy with Azor is not recommended in patients ≥75 years old or with hepatic impairment [See Warnings and Precautions (5.7) and Use in Specific Populations (8.5, 8.6)].

3 DOSAGE FORMS AND STRENGTHS

Azor tablets are formulated for oral administration in the following strength combinations:

 | 5/20 | 5/40 | 10/20 | 10/40
Amlodipine equivalent (mg) | 5 | 5 | 10 | 10
Olmesartan medoxomil (mg) | 20 | 40 | 20 | 40

4 CONTRAINDICATIONS

None.

5 WARNINGS AND PRECAUTIONS

Enter section text here

5.1 Fetal/Neonatal Morbidity and Mortality

Olmesartan medoxomil. Drugs that act directly on the renin-angiotensin system can cause fetal and neonatal morbidity and death when administered to pregnant women. There have been several dozen cases reported in the world literature of patients who were taking angiotensin converting enzyme inhibitors. When pregnancy is detected, discontinue Azor as soon as possible.

During the second and third trimesters of pregnancy, these drugs have been associated with fetal injury that includes hypotension, neonatal skull hypoplasia, anuria, reversible or irreversible renal failure, and death. Oligohydramnios has also been reported, presumably resulting from decreased fetal renal function; oligohydramnios in this setting has been associated with fetal limb contractures, craniofacial deformation, and hypoplastic lung development. Prematurity, intrauterine growth retardation, and patent ductus arteriosus have also been reported, although it is not clear whether these occurrences were due to exposure to the drug.

These adverse effects do not appear to have resulted from intrauterine drug exposure that has been limited to the first trimester. Mothers whose embryos and fetuses are exposed to an angiotensin II receptor antagonist only during the first trimester should be so informed. Nonetheless, when patients become pregnant, physicians should have the patient discontinue the use of Azor as soon as possible.

Rarely (probably less often than once in every thousand pregnancies), no alternative to a drug acting on the renin-angiotensin system will be found. In these rare cases, the mothers should be apprised of the potential hazards to their fetuses and serial ultrasound examinations should be performed to assess the intra-amniotic environment.

If oligohydramnios is observed, discontinue Azor unless it is considered life-saving for the mother. Contraction stress testing (CST), a non-stress test (NST), or biophysical profiling (BPP) may be appropriate, depending upon the week of pregnancy. Patients and physicians should be aware, however, that oligohydramnios may not appear until after the fetus has sustained irreversible injury.

Infants with histories of in utero exposure to an angiotensin II receptor antagonist should be closely observed for hypotension, oliguria, and hyperkalemia. If oliguria occurs, attention should be directed toward support of blood pressure and renal perfusion. Exchange transfusion or dialysis may be required as means of reversing hypotension and/or substituting for disordered renal function.

No teratogenic effects were observed when olmesartan medoxomil was administered to pregnant rats at oral doses up to 1000 mg/kg/day (240 times the maximum recommended human dose (MRHD) on a mg/m^2 basis) or pregnant rabbits at oral doses up to 1 mg/kg/day (half the MRHD on a mg/m^2 basis; higher doses could not be evaluated for effects on fetal development as they were lethal to the does). In rats, significant decreases in pup birth weight and weight gain were observed at doses ≥1.6 mg/kg/day, and delays in developmental milestones (delayed separation of ear auricular, eruption of lower incisors, appearance of abdominal hair, descent of testes, and separation of eyelids) and dose-dependent increases in the incidence of dilation of the renal pelvis were observed at doses ≥8 mg/kg/day. The no observed effect dose for developmental toxicity in rats is 0.3 mg/kg/day, about one-tenth the MRHD of 40 mg/day.

5.2 Hypotension in Volume- or Salt-Depleted Patients

Olmesartan medoxomil. Symptomatic hypotension may be anticipated after initiation of treatment with olmesartan medoxomil. Patients with an activated renin-angiotensin system, such as volume- and/or salt-depleted patients (e.g., those being treated with high doses of diuretics) may be particularly vulnerable. Initiate treatment with Azor under close medical supervision. If hypotension does occur, place the patient in the supine position and, if necessary, give an intravenous infusion of normal saline. A transient hypotensive response is not a contraindication to further treatment, which usually can be continued without difficulty once the blood pressure has stabilized.

5.3 Vasodilation

Amlodipine. Since the vasodilation attributable to amlodipine in Azor is gradual in onset, acute hypotension has rarely been reported after oral administration. Nonetheless, exercise caution, as with any other peripheral vasodilator, when administering Azor, particularly in patients with severe aortic stenosis.

5.4 Patients with Severe Obstructive Coronary Artery Disease

Patients, particularly those with severe obstructive coronary artery disease, may develop increased frequency, duration, or severity of angina or acute myocardial infarction on starting calcium channel blocker therapy or at the time of dosage increase. The mechanism of this effect has not been elucidated.

5.5 Patients with Congestive Heart Failure

Amlodipine. In general, calcium channel blockers should be used with caution in patients with heart failure. Amlodipine (5-10 mg per day) has been studied in a placebo-controlled trial of 1153 patients with NYHA Class III or IV heart failure on stable doses of ACE inhibitor, digoxin, and diuretics. Follow-up was at least 6 months, with a mean of about 14 months. There was no overall adverse effect on survival or cardiac morbidity (as defined by life-threatening arrhythmia, acute myocardial infarction, or hospitalization for worsened heart failure). Amlodipine has been compared to placebo in four 8-12 week studies of patients with NYHA class II/III heart failure, involving a total of 697 patients. In these studies, there was no evidence of worsening of heart failure based on measures of exercise tolerance, NYHA classification, symptoms, or LVEF.

5.6 Patients with Impaired Renal Function

Azor. There are no studies of Azor in patients with renal impairment.

Olmesartan medoxomil. Changes in renal function may be anticipated in susceptible individuals treated with olmesartan medoxomil as a consequence of inhibiting the renin-angiotensin-aldosterone system. In patients whose renal function may depend upon the activity of the renin-angiotensin-aldosterone system (e.g., patients with severe congestive heart failure), treatment with angiotensin converting enzyme inhibitors and angiotensin receptor antagonists has been associated with oliguria or progressive azotemia and (rarely) with acute renal failure and/or death. Similar effects may occur in patients treated with Azor because of the olmesartan medoxomil component [See Clinical Pharmacology (12.3)].

In studies of ACE inhibitors in patients with unilateral or bilateral renal artery stenosis, increases in serum creatinine or blood urea nitrogen (BUN) have been reported. There has been no long-term use of olmesartan medoxomil in patients with unilateral or bilateral renal artery stenosis, but similar effects would be expected with olmesartan medoxomil and Azor.

5.7 Patients with Hepatic Impairment

Amlodipine. Since amlodipine is extensively metabolized by the liver and the plasma elimination half-life (t1/2) is 56 hours in patients with severely impaired hepatic function, exercise caution when administering Azor to patients with severe hepatic impairment.

Patients with hepatic impairment have decreased clearance of amlodipine. Starting amlodipine or adding amlodipine at 2.5 mg in hepatically impaired patients is recommended. The lowest dose of Azor is 5/20 mg; therefore, initial therapy with Azor is not recommended in hepatically impaired patients [See Use in Specific Populations (8.6)].

5.8 Laboratory Tests

Azor. There was a greater decrease in hemoglobin and hematocrit in the combination product compared to either component. Other laboratory changes can usually be attributed to either monotherapy component.

Amlodipine. In post-marketing experience, hepatic enzyme elevations have been reported (6.2).

Olmesartan medoxomil. In post-marketing experience, increased blood creatinine levels and hyperkalemia have been reported.

6 ADVERSE REACTIONS

Enter section text here

6.1 Clinical Trials Experience

Because clinical studies are conducted under widely varying conditions, adverse reaction rates observed in the clinical studies of a drug cannot be directly compared to rates in the clinical studies of another drug and may not reflect the rates observed in practice.

Azor

The data described below reflect exposure to Azor in more than 1600 patients including more than 1000 exposed for at least 6 months and more than 700 exposed for 1 year. Azor was studied in one placebo-controlled factorial trial (see Section 14.1). The population had a mean age of 54 years and included approximately 55% males. Seventy-one percent were Caucasian and 25% were Black. Patients received doses ranging from 5/20 mg to 10/40 mg orally once daily.

The overall incidence of adverse reactions on therapy with Azor was similar to that seen with corresponding doses of the individual components of Azor, and to placebo. The reported adverse reactions were generally mild and seldom led to discontinuation of treatment (2.6% for Azor and 6.8% for placebo).

Edema

Edema is a known, dose-dependent adverse effect of amlodipine but not of olmesartan medoxomil.

The placebo-subtracted incidence of edema during the 8-week, randomized, double-blind treatment period was highest with amlodipine 10 mg monotherapy. The incidence was significantly reduced when 20 mg or 40 mg of olmesartan medoxomil was added to the 10 mg amlodipine dose.

Placebo-Subtracted Incidence of Edema during the Double-Blind Treatment Period
 | Olmesartan Medoxomil
 | Placebo | 20 mg | 40 mg
Amlodipine | Placebo | –%* | -2.4% | 6.2%
5mg | 0.7% | 5.7% | 6.2%
10 mg | 24.5% | 13.3% | 11.2%

*12.3% = actual placebo incidence

Across all treatment groups, the frequency of edema was generally higher in women than men, as has been observed in previous studies of amlodipine.

Adverse reactions seen at lower rates during the double-blind period also occurred in the patients treated with Azor at about the same or greater incidence as in patients receiving placebo. These included hypotension, orthostatic hypotension, rash, pruritus, palpitation, urinary frequency, and nocturia.

The adverse event profile obtained from 44 weeks of open-label combination therapy with amlodipine plus olmesartan medoxomil was similar to that observed during the 8-week, double-blind, placebo-controlled period.

Initial Therapy

Analyzing the data described above specifically for initial therapy, it was observed that higher doses of Azor caused slightly more hypotension and orthostatic symptoms, but not at the recommended starting dose of Azor 5/20 mg. No increase in the incidence of syncope or near syncope was observed. The incidences of discontinuation because of any treatment emergent adverse events in the double blind phase are summarized in the table below.

Discontinuation for any Treatment Emergent Adverse Event^1
 | Olmesartan Medoxomil
 | Placebo | 10 mg | 20 mg | 40 mg
Amlodipine | Placebo | 4.9% | 4.3% | 5.6% | 3.1%
5mg | 3.7% | 0.0% | 1.2% | 3.7%
10 mg | 5.5% | 6.8% | 2.5% | 5.6%

*^1Hypertension is counted as treatment failure and not as treatment emergent adverse event.
N=160-163 subjects per treatment group.
Amlodipine

Amlodipine has been evaluated for safety in more than 11,000 patients in U.S. and foreign clinical trials. Most adverse reactions reported during therapy with amlodipine were of mild or moderate severity. In controlled clinical trials directly comparing amlodipine (N=1730) in doses up to 10 mg to placebo (N=1250), discontinuation of amlodipine due to adverse reactions was required in only about 1.5% of amlodipine-treated patients and about 1% of placebo-treated patients. The most common side effects were headache and edema. The incidence (%) of dose-related side effects was as follows:

Adverse Event | Placebo N=520 | 2.5 mg N=275 | 5.0 mg N=296 | 10.0 mg N=268
Edema | 0.6 | 1.8 | 3.0 | 10.8
Dizziness | 1.5 | 1.1 | 3.4 | 3.4
Flushing | 0.0 | 0.7 | 1.4 | 2.6
Palpitation | 0.6 | 0.7 | 1.4 | 4.5

For several adverse experiences that appear to be drug- and dose-related, there was a greater incidence in women than men associated with amlodipine treatment as shown in the following table;

Adverse Event | Placebo | Amlodipine
 | Male=% (N=914) | Female=% (N=336) | Male=% (N=1218) | Female=% (N=512)
Edema | 1.4 | 5.1 | 5.6 | 14.6
Flushing | 0.3 | 0.9 | 1.5 | 4.5
Palpitation | 0.9 | 0.9 | 1.4 | 3.3
Somnolence | 0.8 | 0.3 | 1.3 | 1.6

Olmesartan medoxomil

Olmesartan medoxomil has been evaluated for safety in more than 3825 patients/subjects, including more than 3275 patients treated for hypertension in controlled trials. This experience included about 900 patients treated for at least 6 months and more than 525 for at least 1 year. Treatment with olmesartan medoxomil was well tolerated, with an incidence of adverse events similar to that seen with placebo. Events were generally mild, transient, and without relationship to the dose of olmesartan medoxomil.

The overall frequency of adverse events was not dose-related. Analysis of gender, age, and race groups demonstrated no differences between olmesartan medoxomil- and placebo-treated patients. The rate of withdrawals due to adverse events in all trials of hypertensive patients was 2.4% (i.e., 79/3278) of patients treated with olmesartan medoxomil and 2.7% (i.e., 32/1179) of control patients. In placebo-controlled trials, the only adverse event that occurred in more than 1% of patients treated with olmesartan medoxomil and at a higher incidence in olmesartan medoxomil treated patients vs. placebo was dizziness (3% vs 1%).

6.2 Post-Marketing Experience

The following adverse reactions have been identified during post-approval use of the individual components of Azor. Because these reactions are reported voluntarily from a population of uncertain size, it is not always possible to reliably estimate their frequency or establish a causal relationship to drug exposure.

Amlodipine. The following post-marketing event has been reported infrequently where a causal relationship is uncertain: gynecomastia. In post-marketing experience, jaundice and hepatic enzyme elevations (mostly consistent with cholestasis or hepatitis), in some cases severe enough to require hospitalization, have been reported in association with use of amlodipine.

Olmesartan medoxomil. The following adverse reactions have been reported in post-marketing experience:

Body as a Whole: asthenia, angioedema
Gastrointestinal: vomiting
Musculoskeletal: rhabdomyolysis
Urogenital System: acute renal failure
Skin and Appendages: alopecia, pruritus, urticaria

7 DRUG INTERACTIONS

Enter section text here

7.1 Drug Interactions with Azor

The pharmacokinetics of amlodipine and olmesartan medoxomil are not altered when the drugs are co-administered.

No drug interaction studies have been conducted with Azor and other drugs, although studies have been conducted with the individual amlodipine and olmesartan medoxomil components of Azor, as described below, and no significant drug interactions have been observed.

7.2 Drug Interactions with Amlodipine

In vitro data indicate that amlodipine has no effect on the human plasma protein binding of digoxin, phenytoin, warfarin, and indomethacin.

Effect of Other Agents on Amlodipine

Cimetidine: Co-administration of amlodipine with cimetidine did not alter the pharmacokinetics of amlodipine.
Grapefruit juice: Co-administration of 240 mL of grapefruit juice with a single oral dose of amlodipine 10 mg in 20 healthy volunteers had no significant effect on the pharmacokinetics of amlodipine.
Maalox® (antacid): Co-administration of the antacid Maalox® with a single dose of amlodipine had no significant effect on the pharmacokinetics of amlodipine.
Sildenafil: A single 100 mg dose of sildenafil in subjects with essential hypertension had no effect on the pharmacokinetic parameters of amlodipine. When amlodipine and sildenafil were used in combination, each agent independently exerted its own blood pressure lowering effect.

Effect of Amlodipine on Other Agents

Atorvastatin: Co-administration of multiple 10 mg doses of amlodipine with 80 mg of atorvastatin resulted in no significant change in the steady state pharmacokinetic parameters of atorvastatin.
Digoxin: Co-administration of amlodipine with digoxin did not change serum digoxin levels or digoxin renal clearance in normal volunteers.
Ethanol (alcohol): Single and multiple 10 mg doses of amlodipine had no significant effect on the pharmacokinetics of ethanol.
Warfarin: Co-administration of amlodipine with warfarin did not change the warfarin prothrombin response time.

In clinical trials, amlodipine has been safely administered with thiazide diuretics, beta-blockers, angiotensin-converting enzyme inhibitors, long-acting nitrates, sublingual nitroglycerin, digoxin, warfarin, non-steroidal anti-inflammatory drugs, antibiotics, and oral hypoglycemic drugs.

7.3 Drug Interactions with Olmesartan Medoxomil

No significant drug interactions were reported in studies in which olmesartan medoxomil was co-administered with digoxin or warfarin in healthy volunteers.

The bioavailability of olmesartan medoxomil was not significantly altered by the co-administration of antacids [Al(OH)3/Mg(OH)2].

Olmesartan medoxomil is not metabolized by the cytochrome P450 system and has no effects on P450 enzymes; thus, interactions with drugs that inhibit, induce, or are metabolized by those enzymes are not expected.

8 USE IN SPECIFIC POPULATIONS

Enter section text here

8.1 Pregnancy

Olmesartan medoxomil. Pregnancy Categories C (first trimester) and D (second and third trimesters). [See Warnings and Precautions (5.1)].

Amlodipine. No evidence of teratogenicity or other embryo/fetal toxicity was found when pregnant rats and rabbits were treated orally with amlodipine maleate at doses of up to 10 mg amlodipine/kg/day (respectively about 10 and 20 times the maximum recommended human dose of 10 mg amlodipine on a mg/m^2 basis) during their respective periods of major organogenesis. (Calculations based on a patient weight of 60 kg). However, litter size was significantly decreased (by about 50%) and the number of intrauterine deaths was significantly increased (about 5-fold) in rats receiving amlodipine maleate at a dose equivalent to 10 mg amlodipine/kg/day for 14 days before mating and throughout mating and gestation. Amlodipine maleate has been shown to prolong both the gestational period and the duration of labor in rats at this dose. There are no adequate and well-controlled studies in pregnant women. Amlodipine should be used during pregnancy only if the potential benefit justifies the potential risk to the fetus.

8.3 Nursing Mothers

It is not known whether the amlodipine or olmesartan medoxomil components of Azor are excreted in human milk, but olmesartan is secreted at low concentration in the milk of lactating rats. Because of the potential for adverse effects on the nursing infant, a decision should be made whether to discontinue nursing or discontinue the drug, taking into account the importance of the drug to the mother.

8.4 Pediatric Use

The safety and effectiveness of Azor in pediatric patients have not been established.

Amlodipine. The effect of amlodipine on blood pressure in patients less than 6 years of age is not known.

Olmesartan medoxomil. Safety and effectiveness of olmesartan medoxomil in pediatric patients have not been established.

8.5 Geriatric Use

Of the total number of subjects in the double-blind clinical study of Azor, 20% (384/1940) were 65 years of age or older and 3% (62/1940) were 75 years or older. No overall differences in safety or effectiveness were observed between subjects 65 years of age or older and younger subjects.

Elderly patients have decreased clearance of amlodipine. Starting amlodipine or adding amlodipine at 2.5 mg in patients ≥75 years old is recommended. The lowest dose of Azor is 5/20 mg; therefore, initial therapy with Azor is not recommended in patients ≥75 years old.

Amlodipine. Reported clinical experience has not identified differences in responses between the elderly and younger patients. In general, dose selection for an elderly patient should be cautious, usually starting at the low end of the dosing range, reflecting the greater frequency of decreased hepatic, renal, or cardiac function, and of concomitant disease or other drug therapy. Elderly patients have decreased clearance of amlodipine with a resulting increase of AUC of approximately 40% to 60%, and a lower initial dose may be required.

Olmesartan medoxomil. Of the total number of hypertensive patients receiving olmesartan medoxomil in clinical studies, more than 20% were 65 years of age and over, while more than 5% were 75 years of age and older. No overall differences in effectiveness or safety were observed between elderly patients and younger patients. Other reported clinical experience has not identified differences in responses between the elderly and younger patients, but greater sensitivity of some older individuals cannot be ruled out.

8.6 Hepatic Impairment

There are no studies of Azor in patients with hepatic insufficiency, but both amlodipine and olmesartan medoxomil show moderate increases in exposure in patients with hepatic impairment. Use caution when administering Azor to patients with severe hepatic impairment.

Patients with hepatic impairment have decreased clearance of amlodipine. Starting amlodipine or adding amlodipine at 2.5 mg in patients with hepatic impairment is recommended. The lowest dose of Azor is 5/20 mg; therefore, initial therapy with Azor is not recommended in hepatically impaired patients.

8.7 Renal Impairment

There are no studies of Azor in patients with renal impairment.

Amlodipine. The pharmacokinetics of amlodipine are not significantly influenced by renal impairment. Patients with renal failure may therefore receive the usual initial dose.

Olmesartan medoxomil. Patients with renal insufficiency have elevated serum concentrations of olmesartan compared with patients with normal renal function. After repeated dosing, AUC was approximately tripled in patients with severe renal impairment (creatinine clearance <20 mL/min). No initial dosage adjustment is recommended for patients with moderate to marked renal impairment (creatinine clearance <40 mL/min).

8.8 Black Patients

Of the total number of subjects in the double-blind clinical study of Azor, 25% (481/1940) were black patients. Azor was effective in treating black patients (usually a low-renin population), and the magnitude of blood pressure reduction in black patients approached that observed for non-black patients.

10 OVERDOSAGE

There is no information on overdosage with Azor in humans.

Amlodipine. Single oral doses of amlodipine maleate equivalent to 40 mg amlodipine/kg and 100 mg amlodipine/kg in mice and rats, respectively, caused deaths. Single oral amlodipine maleate doses equivalent to 4 or more mg amlodipine/kg or higher in dogs (11 or more times the maximum recommended human dose on a mg/m^2 basis) caused a marked peripheral vasodilation and hypotension.

Overdosage might be expected to cause excessive peripheral vasodilation with marked hypotension and possibly a reflex tachycardia. In humans, experience with intentional overdosage of amlodipine is limited.

If massive overdose should occur, active cardiac and respiratory monitoring should be instituted. Frequent blood pressure measurements are essential. Should hypotension occur, cardiovascular support including elevation of the extremities and the judicious administration of fluids should be initiated. If hypotension remains unresponsive to these conservative measures, administration of vasopressors (such as phenylephrine) should be considered with attention to circulating volume and urine output. Intravenous calcium gluconate may help to reverse the effects of calcium entry blockade. As amlodipine is highly protein bound, hemodialysis is not likely to be of benefit.

Olmesartan medoxomil. Limited data are available related to overdosage in humans. The most likely manifestations of overdosage would be hypotension and tachycardia; bradycardia could be encountered if parasympathetic (vagal) stimulation occurs. If symptomatic hypotension should occur, supportive treatment should be initiated. The dialyzability of olmesartan is unknown.

11 DESCRIPTION

Azor is a combination of the calcium channel receptor blocker (CCB) amlodipine besylate and the angiotensin II receptor blocker (ARB) olmesartan medoxomil.

The amlodipine besylate component of Azor is chemically described as 3-ethyl-5-methyl (±)-2-[(2-aminoethoxy)methyl]-4-(2-chlorophenyl)-1,4-dihydro-6-methyl-3,5-pyridinedicarboxylate, monobenzenesulphonate. Its empirical formula is C20H25CIN2O5•C6H6O3S.

Olmesartan medoxomil, a prodrug, is hydrolyzed to olmesartan during absorption from the gastrointestinal tract.

The olmesartan medoxomil component of Azor is chemically described as 2,3-dihydroxy-2-butenyl 4-(1-hydroxy-1-methylethyl)-2-propyl-1-[p-(o-1H-tetrazol-5-ylphenyl)benzyl]imidazole-5-carboxylate, cyclic 2,3-carbonate. Its empirical formula is C29H30N6O6.

The structural formula for amlodipine besylate is:

The structural formula for olmesartan medoxomil is:

Azor contains amlodipine besylate, a white to off-white crystalline powder, and olmesartan medoxomil, a white to light yellowish-white powder or crystalline powder. The molecular weights of amlodipine besylate and olmesartan medoxomil are 567.1 and 558.59, respectively. Amlodipine besylate is slightly soluble in water and sparingly soluble in ethanol. Olmesartan medoxomil is practically insoluble in water and sparingly soluble in methanol.

Each tablet of Azor also contains the following inactive ingredients: silicified microcrystalline cellulose, pregelatinized starch, croscarmellose sodium, and magnesium stearate. The color coatings contain polyvinyl alcohol, macrogol/polyethylene glycol 3350, titanium dioxide, talc, iron oxide yellow (5/40 mg, 10/20 mg, 10/40 mg tablets), iron oxide red (10/20 mg and 10/40 mg tablets), and iron oxide black (10/20 mg tablets).

12 CLINICAL PHARMACOLOGY

Enter section text here

12.1 Mechanism of Action

Azor. Azor is a combination of two antihypertensive drugs: a dihydropyridine calcium antagonist (calcium ion antagonist or slow-channel blocker), amlodipine besylate, and an angiotensin II receptor blocker, olmesartan medoxomil. The amlodipine component of Azor inhibits the transmembrane influx of calcium ions into vascular smooth muscle and cardiac muscle, and the olmesartan medoxomil component of Azor blocks the vasoconstrictor effects of angiotensin II.

Amlodipine. Experimental data suggests that amlodipine binds to both dihydropyridine and nonhydropyridine binding sites. The contractile processes of cardiac muscle and vascular smooth muscle are dependent upon the movement of extracellular calcium ions into these cells through specific ion channels. Amlodipine inhibits calcium ion influx across cell membranes selectively, with a greater effect on vascular smooth muscle cells than on cardiac muscle cells. Negative inotropic effects can be detected in vitro but such effects have not been seen in intact animals at therapeutic doses. Serum calcium concentration is not affected by amlodipine. Within the physiologic pH range, amlodipine is an ionized compound (pKa=8.6), and its kinetic interaction with the calcium channel receptor is characterized by a gradual rate of association and dissociation with the receptor binding site, resulting in a gradual onset of effect.

Amlodipine is a peripheral arterial vasodilator that acts directly on vascular smooth muscle to cause a reduction in peripheral vascular resistance and reduction in blood pressure.

Olmesartan medoxomil. Angiotensin II is formed from angiotensin I in a reaction catalyzed by angiotensin converting enzyme (ACE, kininase II). Angiotensin II is the principal pressor agent of the renin-angiotensin system, with effects that include vasoconstriction, stimulation of synthesis and release of aldosterone, cardiac stimulation and renal reabsorption of sodium. Olmesartan blocks the vasoconstrictor effects of angiotensin II by selectively blocking the binding of angiotensin II to the AT1 receptor in vascular smooth muscle. Its action is, therefore, independent of the pathways for angiotensin II synthesis.

An AT2 receptor is found also in many tissues, but this receptor is not known to be associated with cardiovascular homeostasis. Olmesartan has more than a 12,500-fold greater affinity for the AT1 receptor than for the AT2 receptor.

Blockade of the renin-angiotensin system with ACE inhibitors, which inhibit the biosynthesis of angiotensin II from angiotensin I, is a mechanism of many drugs used to treat hypertension. ACE inhibitors also inhibit the degradation of bradykinin, a reaction also catalyzed by ACE. Because olmesartan does not inhibit ACE (kininase II), it does not affect the response to bradykinin. Whether this difference has clinical relevance is not yet known.

Blockade of the angiotensin II receptor inhibits the negative regulatory feedback of angiotensin II on renin secretion, but the resulting increased plasma renin activity and circulating angiotensin II levels do not overcome the effect of olmesartan on blood pressure.

12.2 Pharmacodynamics

Amlodipine. Following administration of therapeutic doses to patients with hypertension, amlodipine produces vasodilation resulting in a reduction of supine and standing blood pressures. These decreases in blood pressure are not accompanied by a significant change in heart rate or plasma catecholamine levels with chronic dosing.

With chronic once daily oral administration, antihypertensive effectiveness is maintained for at least 24 hours. Plasma concentrations correlate with effect in both young and elderly patients. The magnitude of reduction in blood pressure with amlodipine is also correlated with the height of pretreatment elevation; thus, individuals with moderate hypertension (diastolic pressure 105-114 mmHg) had about a 50% greater response than patients with mild hypertension (diastolic pressure 90-104 mmHg). Normotensive subjects experienced no clinically significant change in blood pressures (+1/-2 mmHg).

In hypertensive patients with normal renal function, therapeutic doses of amlodipine resulted in a decrease in renal vascular resistance and an increase in glomerular filtration rate and effective renal plasma flow without change in filtration fraction or proteinuria.

As with other calcium channel blockers, hemodynamic measurements of cardiac function at rest and during exercise (or pacing) in patients with normal ventricular function treated with amlodipine have generally demonstrated a small increase in cardiac index without significant influence on dP/dt or on left ventricular end diastolic pressure or volume. In hemodynamic studies, amlodipine has not been associated with a negative inotropic effect when administered in the therapeutic dose range to intact animals and man, even when co-administered with beta-blockers to man. Similar findings, however, have been observed in normals or well-compensated patients with heart failure with agents possessing significant negative inotropic effects.

Amlodipine does not change sinoatrial nodal function or atrioventricular conduction in intact animals or man. In clinical studies in which amlodipine was administered in combination with beta-blockers to patients with either hypertension or angina, no adverse effects on electrocardiographic parameters were observed.

Olmesartan medoxomil. Olmesartan medoxomil doses of 2.5 mg to 40 mg inhibit the pressor effects of angiotensin I infusion. The duration of the inhibitory effect was related to dose, with doses of olmesartan medoxomil >40 mg giving >90% inhibition at 24 hours.

Plasma concentrations of angiotensin I and angiotensin II and plasma renin activity (PRA) increase after single and repeated administration of olmesartan medoxomil to healthy subjects and hypertensive patients. Repeated administration of up to 80 mg olmesartan medoxomil had minimal influence on aldosterone levels and no effect on serum potassium.

12.3 Pharmacokinetics

The pharmacokinetics of amlodipine and olmesartan medoxomil from Azor are equivalent to the pharmacokinetics of amlodipine and olmesartan medoxomil when administered separately. The bioavailability of both components is well below 100%, but neither component is affected by food. The effective half-lives of amlodipine (45±11 hours) and olmesartan (7±1 hours) result in a 2- to 3- fold accumulation for amlodipine and negligible accumulation for olmesartan with once-daily dosing.

Amlodipine. After oral administration of therapeutic doses of amlodipine, absorption produces peak plasma concentrations between 6 and 12 hours. Absolute bioavailability is estimated as between 64% and 90%.

Olmesartan medoxomil. Olmesartan medoxomil is rapidly and completely bioactivated by ester hydrolysis to olmesartan during absorption from the gastrointestinal tract. The absolute bioavailability of olmesartan medoxomil is approximately 26%. After oral administration, the peak plasma concentration (Cmax) of olmesartan is reached after 1 to 2 hours. Food does not affect the bioavailability of olmesartan medoxomil.

Distribution

Amlodipine. Ex vivo studies have shown that approximately 93% of the circulating drug is bound to plasma proteins in hypertensive patients. Steady-state plasma levels of amlodipine are reached after 7 to 8 days of consecutive daily dosing.

Olmesartan medoxomil. The volume of distribution of olmesartan is approximately 17 L. Olmesartan is highly bound to plasma proteins (99%) and does not penetrate red blood cells. The protein binding is constant at plasma olmesartan concentrations well above the range achieved with recommended doses.

In rats, olmesartan crossed the blood-brain barrier poorly, if at all. Olmesartan passed across the placental barrier in rats and was distributed to the fetus. Olmesartan was distributed to milk at low levels in rats.

Metabolism and Excretion

Amlodipine. Amlodipine is extensively (about 90%) converted to inactive metabolites via hepatic metabolism. Elimination from the plasma is biphasic with a terminal elimination half-life of about 30 to 50 hours. Ten percent of the parent compound and 60% of the metabolites are excreted in the urine.

Olmesartan medoxomil. Following the rapid and complete conversion of olmesartan medoxomil to olmesartan during absorption, there is virtually no further metabolism of olmesartan. Total plasma clearance of olmesartan is 1.3 L/h, with a renal clearance of 0.6 L/h. Approximately 35% to 50% of the absorbed dose is recovered in urine while the remainder is eliminated in feces via the bile.

Olmesartan appears to be eliminated in a biphasic manner with a terminal elimination half-life of approximately 13 hours. Olmesartan shows linear pharmacokinetics following single oral doses of up to 320 mg and multiple oral doses of up to 80 mg. Steady-state levels of olmesartan are achieved within 3 to 5 days and no accumulation in plasma occurs with once-daily dosing.

Geriatric

The pharmacokinetic properties of Azor in the elderly are similar to those of the individual components.

Amlodipine. Elderly patients have decreased clearance of amlodipine with a resulting increase in AUC of approximately 40% to 60%, and a lower initial dose may be required.

Olmesartan medoxomil. The pharmacokinetics of olmesartan medoxomil were studied in the elderly (>65 years). Overall, maximum plasma concentrations of olmesartan were similar in young adults and the elderly. Modest accumulation of olmesartan was observed in the elderly with repeated dosing; AUCѕѕ, τ was 33% higher in elderly patients, corresponding to an approximate 30% reduction in CLR.

Pediatric

Amlodipine. Sixty-two hypertensive patients aged 6 to 17 years received doses of amlodipine between 1.25 mg and 20 mg. Weight-adjusted clearance and volume of distribution were similar to values in adults.

Olmesartan medoxomil. The pharmacokinetics of olmesartan medoxomil have not been investigated in patients <18 years of age.

Gender

Population pharmacokinetic analysis indicated that female patients had approximately 15% smaller clearances of olmesartan than male patients. Gender had no effect on the clearance of amlodipine.

Olmesartan medoxomil. Minor differences were observed in the pharmacokinetics of olmesartan medoxomil in women compared to men. AUC and Cmax were 10% to 15% higher in women than in men.

Renal Insufficiency

Amlodipine. The pharmacokinetics of amlodipine are not significantly influenced by renal impairment. Patients with renal failure may therefore receive the usual initial dose.

Olmesartan medoxomil. In patients with renal insufficiency, serum concentrations of olmesartan were elevated compared to subjects with normal renal function. After repeated dosing, the AUC was approximately tripled in patients with severe renal impairment (creatinine clearance <20 mL/min). The pharmacokinetics of olmesartan medoxomil in patients undergoing hemodialysis has not been studied. No initial dosage adjustment is recommended for patients with moderate to marked renal impairment (creatinine clearance <40 mL/min).

Hepatic Insufficiency

Amlodipine. Patients with hepatic insufficiency have decreased clearance of amlodipine with a resulting increase in AUC of approximately 40% to 60%.

Olmesartan medoxomil. Increases in AUC0-∞ and Cmax were observed in patients with moderate hepatic impairment compared to those in matched controls, with an increase in AUC of about 60%.

Heart Failure

Amlodipine. Patients with heart failure have decreased clearance of amlodipine with a resulting increase in AUC of approximately 40% to 60%.

13 NONCLINICAL TOXICOLOGY

Enter section text here

13.1 Carcinogenesis, Mutagenesis, Impairment of Fertility

Amlodipine. Rats and mice treated with amlodipine maleate in the diet for up to two years, at concentrations calculated to provide daily dosage levels of amlodipine 0.5, 1.25, and 2.5 mg/kg/day showed no evidence of a carcinogenic effect of the drug. For the mouse, the highest dose was, on a mg/m^2 basis, similar to the maximum recommended human dose (MRHD) of amlodipine 10 mg/day. For the rat, the highest dose was, on a mg/m^2 basis, about two and a half times the MRHD. (Calculations based on a 60 kg patient.)

Mutagenicity studies conducted with amlodipine maleate revealed no drug related effects at either the gene or chromosome level.

There was no effect on the fertility of rats treated orally with amlodipine maleate (males for 64 days and females for 14 days prior to mating) at doses of amlodipine up to 10 mg/kg/day (about 10 times the MRHD of 10 mg/day on a mg/m^2 basis).

Olmesartan medoxomil. Olmesartan was not carcinogenic when administered by dietary administration to rats for up to 2 years. The highest dose tested (2000 mg/kg/day) was, on a mg/m^2 basis, about 480 times the maximum recommended human dose (MRHD) of 40 mg/day. Two carcinogenicity studies conducted in mice, a 6-month gavage study in the p53 knockout mouse and a 6-month dietary administration study in the Hras2 transgenic mouse, at doses of up to 1000 mg/kg/day (about 120 times the MRHD), revealed no evidence of a carcinogenic effect of olmesartan. Both olmesartan medoxomil and olmesartan tested negative in the in vitro Syrian hamster embryo cell transformation assay and showed no evidence of genetic toxicity in the Ames (bacterial mutagenicity) test. However, both were shown to induce chromosomal aberrations in cultured cells in vitro (Chinese hamster lung) and tested positive for thymidine kinase mutations in the in vitro mouse lymphoma assay. Olmesartan medoxomil tested negative in vivo for mutations in the MutaMouse intestine and kidney and for clastogenicity in mouse bone marrow (micronucleus test) at oral doses of up to 2000 mg/kg (olmesartan not tested).

Fertility of rats was unaffected by administration of olmesartan at dose levels as high as 1000 mg/kg/day (240 times the MRHD) in a study in which dosing was begun 2 (female) or 9 (male) weeks prior to mating.

14 CLINICAL STUDIES

Enter section text here

14.1 Azor

An 8-week multicenter, randomized, double-blind, placebo controlled, parallel group factorial study in patients with mild to severe hypertension was conducted to determine if treatment with Azor was associated with clinically significant reduction in blood pressure compared to the respective monotherapies. The study randomized 1940 patients equally to one of the following 12 treatment arms: placebo, monotherapy treatment with amlodipine 5 mg or 10 mg, monotherapy treatment with olmesartan medoxomil 10 mg, 20 mg, or 40 mg, or combination therapy with amlodipine/olmesartan medoxomil at doses of 5/10 mg, 5/20 mg, 5/40 mg, 10/10 mg, 10/20 mg, and 10/40 mg. Patients discontinued their prior antihypertensive treatment. The mean baseline blood pressure of the study population was 164/102 mmHg. Of the total cohort, 970 patients were treated with the combination as initial therapy.

Treatment with Azor resulted in statistically significant greater reductions in diastolic and systolic blood pressure compared to the respective monotherapy components.

The following table presents the results for mean reduction in seated systolic and diastolic blood pressure following 8 weeks of treatment with Azor. Placebo-adjusted reductions from baseline in blood pressure were progressively greater with increases in dose of both amlodipine and olmesartan medoxomil components of Azor.

Reduction in Seated Systolic/Diastolic Blood Pressure (mmHg): Combination Therapy vs. Monotherapy Components (Double-Blind Treatment Period)
 | Olmesartan medoxomil
(mmHg) | Placebo | 10 mg | 20 mg | 40 mg
Amlodipine | Placebo | Mean Change | -5/-3 | -12/-8 | -14/-9 | -16/-10
Placebo-Adjusted Mean Change | -- | -8/-5 | -10/-6 | -13/-7
5 mg | Mean Change | -15/-9 | -24/-14 | -24/-14 | -25/-16
Placebo-Adjusted Mean Change | -12/-7 | -20/-11 | -20/-11 | -22/-13
10mg | Mean Change | -20/-13 | -25/-16 | -29/-17 | -30/-19
Placebo-Adjusted Mean Change | -16/-10 | -22/-13 | -25/-14 | -26/-16

The antihypertensive effect of Azor was similar in patients with and without prior antihypertensive medication use, in patients with and without diabetes, in patients >65 years of age and <65 years of age, and in women and men. Limited data exist in patients >75 years of age.

Azor was effective in treating black patients (usually a low-renin population), and the magnitude of blood pressure reduction in black patients approached that observed for non-Black patients. This effect in black patients has been seen with ACE inhibitors, angiotensin receptor blockers, and beta-blockers.

The blood pressure lowering effect was maintained throughout the 24-hour period with Azor once daily, with trough-to-peak ratios for systolic and diastolic response between 71% and 82%.

Upon completing the 8-week, double-blind, placebo-controlled study, 1684 patients entered a 44-week open-label extension and received combination therapy with amlodipine 5 mg plus olmesartan medoxomil 40 mg. During the open-label extension, patients whose blood pressure was not adequately controlled (i.e., did not achieve a blood pressure goal of <140/90 mmHg, or <130/80 mmHg for those patients with diabetes) on amlodipine/olmesartan medoxomil 5/40 mg were titrated to amlodipine/olmesartan medoxomil 10/40 mg. Patients whose blood pressure was still not adequately controlled were offered additional hydrochlorothiazide 12.5 mg and subsequently 25 mg as required to achieve adequate blood pressure goal.

14.2 Amlodipine

The antihypertensive efficacy of amlodipine has been demonstrated in a total of 15 double-blind, placebo-controlled, randomized studies involving 800 patients on amlodipine and 538 on placebo. Once daily administration produced statistically significant placebo-corrected reductions in supine and standing blood pressures at 24 hours postdose, averaging about 12/6 mmHg in the standing position and 13/7 mmHg in the supine position in patients with mild to moderate hypertension. Maintenance of the blood pressure effect over the 24-hour dosing interval was observed, with little difference in peak and trough effect.

14.3 Olmesartan Medoxomil

The antihypertensive effects of olmesartan medoxomil have been demonstrated in seven placebo-controlled studies at doses ranging from 2.5 mg to 80 mg for 6 to 12 weeks, each showing statistically significant reductions in peak and trough blood pressure. A total of 2693 patients (2145 olmesartan medoxomil; 548 placebo) with essential hypertension were studied. The blood pressure lowering effect was maintained throughout the 24-hour period with olmesartan medoxomil once daily, with trough-to-peak ratios for systolic and diastolic response between 60% and 80%.

16 HOW SUPPLIED/STORAGE AND HANDLING

Azor tablets contain amlodipine besylate at a dose equivalent to 5 or 10 mg amlodipine and olmesartan medoxomil in the strengths described below.

Azor tablets are differentiated by tablet color/size and are debossed with an individual product tablet code on one side. Azor tablets are supplied for oral administration in the following strength and package configurations:

Tablet Strength; (amlodipine equivalent/; olmesartan medoxomil) mg | Package Configuration | NDC# | Product Code | Tablet Color
5/20 mg | Bottle of 30 | 54868-6036-0 | C73 | White
10/40 mg | Bottle of 30 | 54868-6250-0 | C77 | Brownish Red

Store at 25°C (77°F); excursions permitted to 15-30°C (59-86°F) [see USP Controlled Room Temperature].

17 PATIENT COUNSELING INFORMATION

Physicians should instruct female patients of childbearing age about the consequences of second and third trimester exposure to drugs that act on the renin-angiotensin system and they should be told that these consequences do not appear to have resulted from intrauterine drug exposure that has been limited to the first trimester. These patients should be informed to report pregnancies to their physicians as soon as possible. [See Warnings and Precautions (5.1) and Use in Specific Populations (8.1) ].

Manufactured for Daiichi Sankyo, Inc., Parsippany, New Jersey 07054
Manufactured by Daiichi Sankyo Europe GmbH, Germany

Copyright © Daiichi Sankyo, Inc. 2007. All rights reserved.

Relabeling of "Additional" barcode label by: Physicians Total Care, Inc., Tulsa, OK 74146

PRINCIPAL DISPLAY PANEL

5 mg / 20 mg Azor Tablet

10 mg / 40 mg Azor Tablet